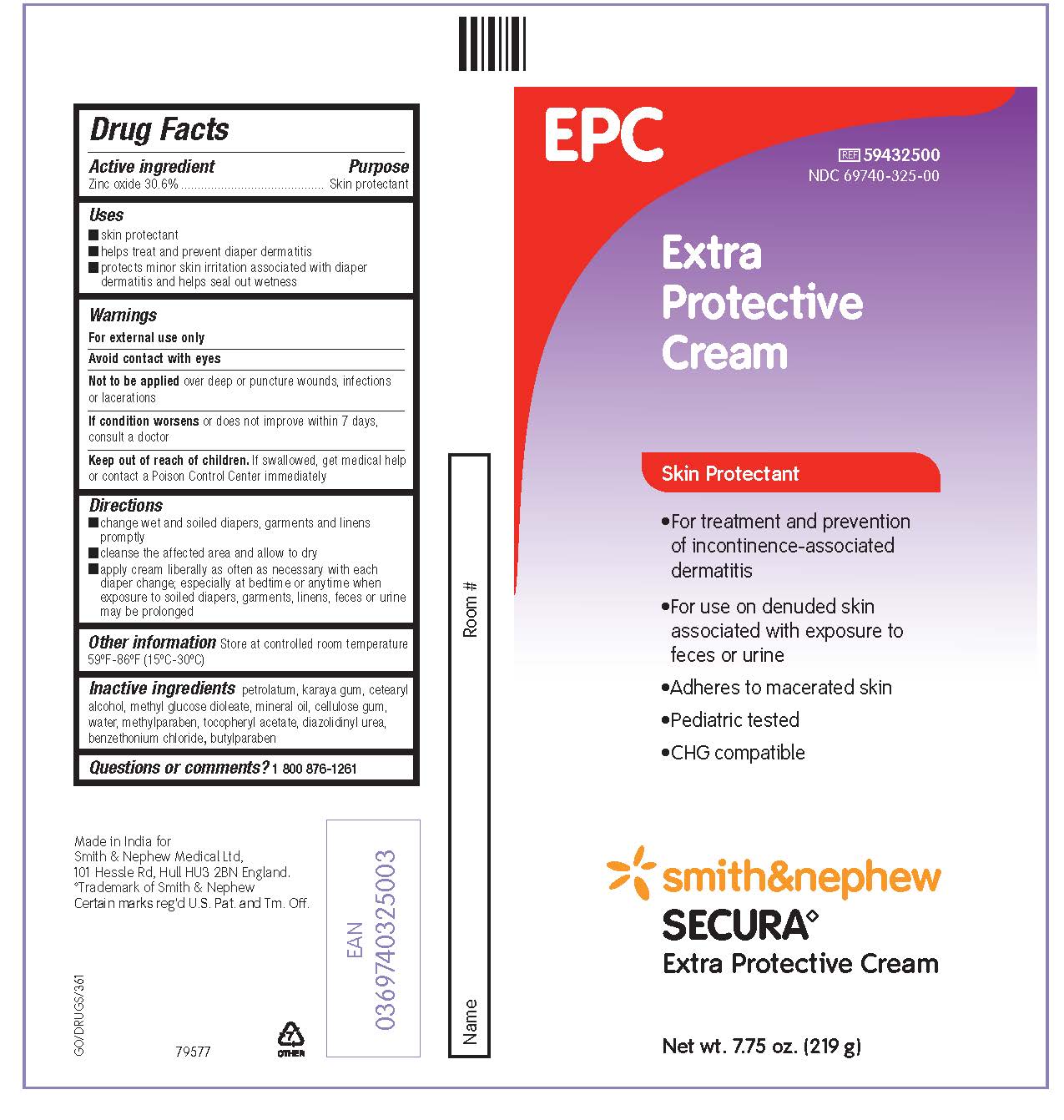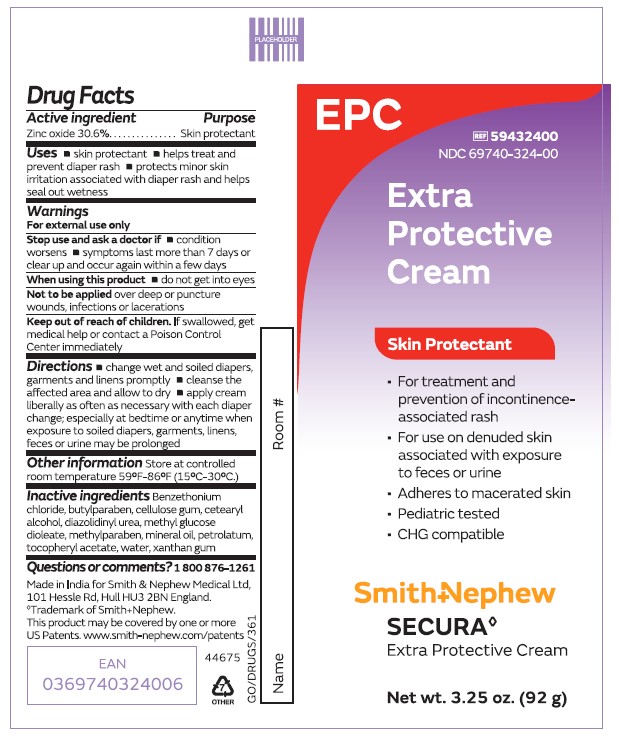 DRUG LABEL: Secura Extra Protective
NDC: 69740-324 | Form: CREAM
Manufacturer: Smith & Nephew Medical Ltd
Category: otc | Type: HUMAN OTC DRUG LABEL
Date: 20250417

ACTIVE INGREDIENTS: ZINC OXIDE 306.1 mg/1 g
INACTIVE INGREDIENTS: CELLULOSE GUM; BENZETHONIUM CHLORIDE; BUTYLPARABEN; DIAZOLIDINYL UREA; XANTHAN GUM; METHYLPARABEN; MINERAL OIL; PETROLATUM; WATER; ALPHA-TOCOPHEROL ACETATE; CETOSTEARYL ALCOHOL; METHYL GLUCOSE DIOLEATE

Secura Extra Protective Cream

ACTIVE INGREDIENT

Zinc Oxide 30.6%

PURPOSE

Skin protectant

USES

- skin protectant
- helps treat and prevent diaper rash
- protects minor skin irritation associated with diaper rash and helps seal out wetness

Update in line with OTC Monograph

Amendment from reference to 'dermatitis' to 'rash'

Apr 2025

WARNINGS

- For external use only
- Stop use and ask a doctor if condition worsens, symptoms last more than 7 days or clears up and occur again within a few days
- When using this product do not get into eyes
- Not to be applied over deep or puncture wounds, infections, or lacerations
- Keep out of reach of children. If swallowed, get medical help or contact a Poison Control Certer immediately

STOP USE

- If condition worsensor does not improve within 7 days, contact a doctor

- Keep out of reach of children.If swallowed, get medical help or contact a Poison Control Center immediately

DIRECTIONS

- change wet and soiled diapers, garments and linens promptly
- cleanse the affected area and allow to dry
- apply cream liberally as often as necessary with each diaper change; especially at bedtime or anytime when exposure to soiled diapers, garments, linens, feces, or urine may be prolonged

OTHER INFORMATION

Store at controlled room temperature 59oF-86oF (15oC-30oC)

INACTIVE INGREDIENTS

benzethonium chloride, butylparaben, cellulose gum, cetearyl alcohol, diazolidinyl urea, methyl glucose dioleate, methylparaben, mineral oil, petrolatum, tocopheryl acetate, water, xanthan gum.

QUESTIONS OR COMMENTS?

1 800 876-1261

PACKAGE LABEL - PRINCIPAL DISPLAY PANEL- TUBE (92g)

Item #59432400

NDC 69740-324-00

Extra Protective Cream

Skin Protectant

- For treatment and prevention of incontinence-associated dermatitis
- For use on denuded skin associated with exposure to feces or urine
- Adheres to macerated skin
- Pediatric tested
- CHG compatible

Smith & Nephew

Secura◊

Extra Protective Cream

Made in India for
Smith & Nephew Medical Ltd, 101 Hessle Road, Hull, HU3 2BN, England

◊Trademark of Smith & Nephew

Certain marks reg'd U.S. Pat. and Tm. Off.

PACKAGE LABEL - PRINCIPAL DISPLAY PANEL- TUBE (219g)

Item #59432500

NDC69740-325-00

Extra Protective Cream

Skin Protectant

- For treatment and prevention of incontinence-associated dermatitis
- For use on denuded skin associated with exposure to feces or urine
- Adheres to macerated skin
- Pediatric tested
- CHG compatible

Smith & Nephew

Secura◊

Extra Protective Cream

Made in India for
Smith & Nephew Medical Ltd, 101 Hessle Road, Hull, HU3 2BN, England

◊Trademark of Smith & Nephew

Certain marks reg'd U.S. Pat. and Tm. Off.